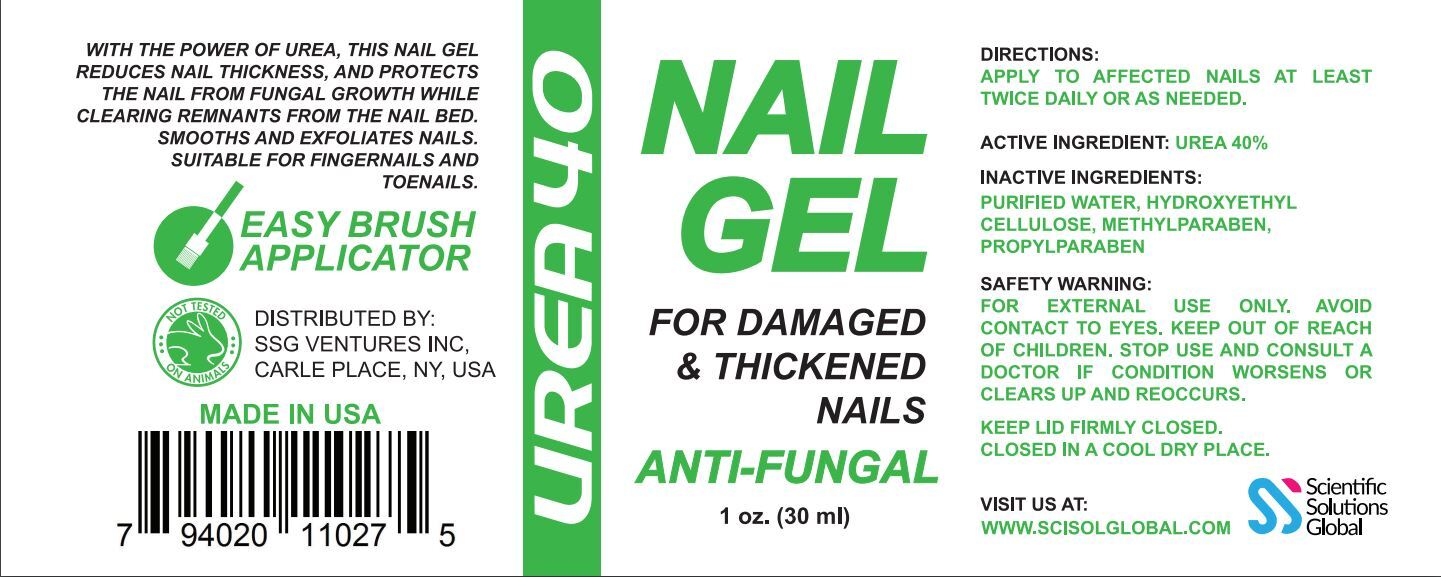 DRUG LABEL: Urea 40 Nail Gel
NDC: 81376-600 | Form: GEL
Manufacturer: SSG Ventures Inc
Category: otc | Type: HUMAN OTC DRUG LABEL
Date: 20210209

ACTIVE INGREDIENTS: UREA 12 g/12 g
INACTIVE INGREDIENTS: WATER; DIMETHYL SULFOXIDE; HYDROXYETHYL CELLULOSE (100 MPA.S AT 2%)

Urea 40 Nail Gel

PACKAGE LABEL

ACTIVE INGREDIENT

Urea

PURPOSE

FOR DAMAGED & THICKENED NAILS

ANTI-FUNGAL

INDICATIONS AND USAGE

WITH THE POWER OF UREA, THIS NAIL GEL REDUCES NAIL THICKNEDD AND PROTECTS THE NAIL FROM FUNGAL GROWTH WHILE CLEARING THE REMNANTS FROM THE NAIL BED.

SMOOTHS ANS EXFOLIATES NAILS.

SUITABLE FOR FINGERNAILS AND TOENAILS.

SAFE HANDLING WARNING

FOR EXTERNAL USE ONLY.

AVOID CONTACT TO EYES.

KEEP OUT OF REACH OF CHILDREN.

STOP USE AND CONSULT A DOCTOR IF CONDITION WORSENS OR CLEARS UP AND REOCCURS

KEEP LID FIRMLY CLOSED.

CLOSED IN A COOL DRY PLACE

KEEP OUT OF REACH OF CHILDREN

DOSAGE AND ADMINISTRATION

APPLY TO AFFECTED NAILS AT LEAST TWICE DAILY OR AS NEEDED

INACTIVE INGREDIENT

HYDROXYETHYL CELLULOSE NF, PURIFIED WATER, DIMETHYL SULFOXIDE USP

STORAGE AND HANDLING

KEEP LID FIRMLY CLOSED

CLOSED IN A COOL DRY PLACE

WARNINGS

FOR EXTERNAL USE ONLY.

AVOID CONTACT TO EYES.

KEEP OUT OF REACH OF CHILDREN

STOP USE AND CONSULT DOCTOR IF CONDITION WORSENS OR CLEARS US AND REOCCURS